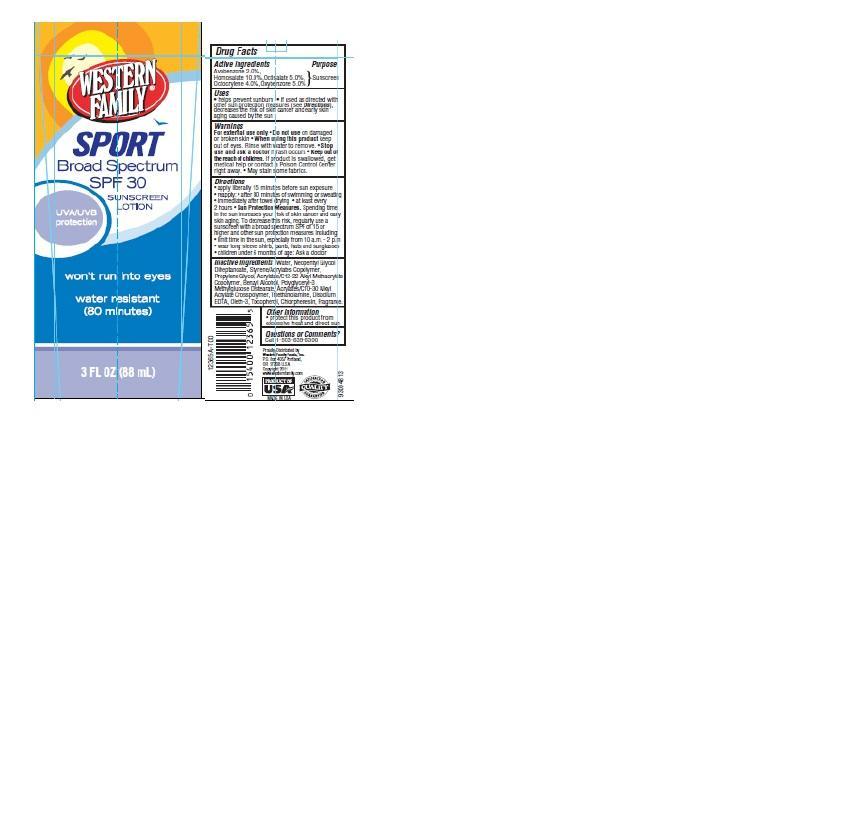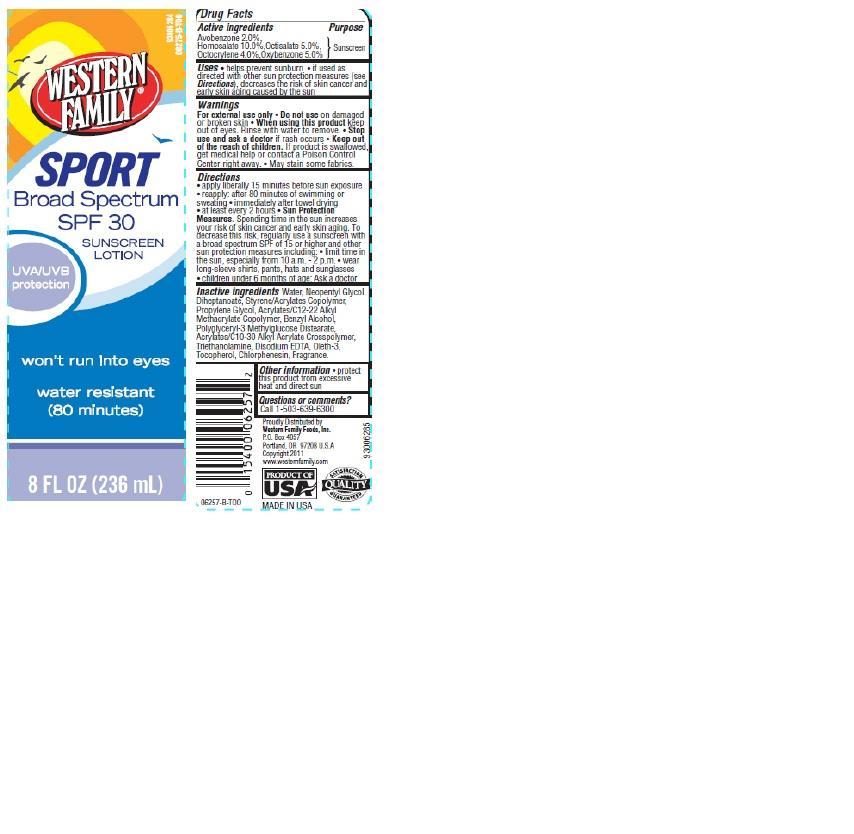 DRUG LABEL: Western Family Sport Sunscreen
NDC: 55312-005 | Form: LOTION
Manufacturer: WESTERN FAMILY FOODS, INC.
Category: otc | Type: HUMAN OTC DRUG LABEL
Date: 20140702

ACTIVE INGREDIENTS: AVOBENZONE 2 g/100 g; HOMOSALATE 10 g/100 g; OCTISALATE 5 g/100 g; OCTOCRYLENE 4 g/100 g; OXYBENZONE 5 g/100 g
INACTIVE INGREDIENTS: WATER; NEOPENTYL GLYCOL DIHEPTANOATE; PROPYLENE GLYCOL; TROLAMINE; CHLORPHENESIN; BENZYL ALCOHOL; OLETH-3; TOCOPHEROL; EDETATE DISODIUM

Drug Facts

Active ingredients

Avobenzone 2.0 %

Homosalate 10.0%

Octisalate 5.0%

Octocrylene 4.0%

Oxybenzone 5.0%

Purpose

Sunscreen

Uses

- Helps prevent sunburn
- If used as directed with other sun protection measures (see Directions), decrease the risk of skin cancer and early skin aging caused by the sun.

Warnings

For external use only

When using this product

- keep out of eyes. Rinse with water to remove.

Stop use and ask a doctor if

- rash or irritation develops and lasts

Keep out of reach of children.

If swallowed get medical help or contact a Poison Control Center right away.

Other information

- protect this product from excessive heat and direct sun

Directions

- apply liberally 15 minutes before sun exposure
- reapply
- after 80 minutes of swimming or sweating
- immediately after towel drying
- at least every 2 hours
- Sun Protection Measures: Spending time in the sun increases your risk of skin cancer and early skin aging. To decrease this risk, regularly use a sunscreen with a broad spectrum SPF of 15 or higher and other sun protection measures including:
- limit time in the sun, especially from 10 a.m. - 2 p.m.
- wear long-sleeve shirts, pants, hats and sunglasses
- children under 6 months of age: Ask a doctor

Inactive ingredients

Water, Neopentyl Glycol Diheptanoate, Styrene/Acrylates Copolymer, Propylene Glycol, Polyglyceryl-3 Methylglucose Distearate, Benzyl Alcohol, Acrylates/C10-30 Alkyl Acrylate Crosspolymer, Triethanolamine, Disodium EDTA, Oleth-3, Tocopherol, Chlorphenesin, Fragrance.

Principal Display Panel

WESTERN FAMILY

SPORT

Broad Spectrum SPF 30

SUNSCREEN LOTION

UVA/UVB protection

Wont Run into Eyes

Water Resistant (80 Minutes)

3 FL OZ (88 mL)

WESTERN FAMILY

SPORT

Broad Spectrum SPF 30

SUNSCREEN LOTION

UVA/UVB protection

Wont Run into Eyes

Water Resistant (80 Minutes)

8 FL OZ (236 mL)

Questions or comments?

Call 1-503-639-6300